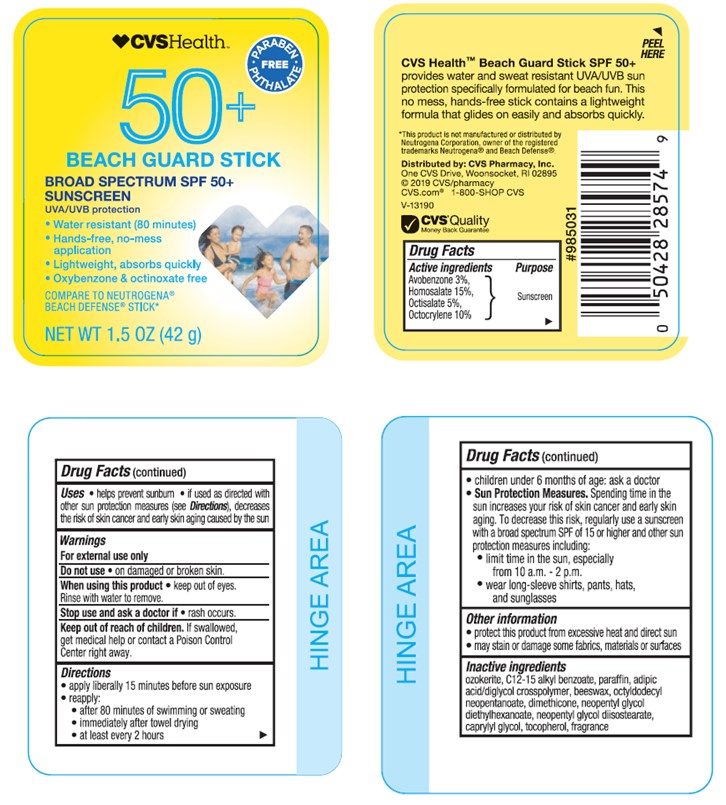 DRUG LABEL: CVS Health SPF 50 Beach Guard
NDC: 69842-526 | Form: STICK
Manufacturer: CVS Pharmacy
Category: otc | Type: HUMAN OTC DRUG LABEL
Date: 20241022

ACTIVE INGREDIENTS: OCTOCRYLENE 100 mg/1 g; HOMOSALATE 150 mg/1 g; AVOBENZONE 30 mg/1 g; OCTISALATE 50 mg/1 g
INACTIVE INGREDIENTS: CERESIN; ALKYL (C12-15) BENZOATE; PARAFFIN; ADIPIC ACID/DIGLYCOL CROSSPOLYMER (20000 MPA.S); WHITE WAX; OCTYLDODECYL NEOPENTANOATE; DIMETHICONE; NEOPENTYL GLYCOL DIETHYLHEXANOATE; NEOPENTYL GLYCOL DIISOSTEARATE; CAPRYLYL GLYCOL; .ALPHA.-TOCOPHEROL, DL-

CVS Health SPF 50+ Beach Guard Stick

Active ingredients

Avobenzone 3.0%, Homosalate 15.0%, Octisalate 5.0%, Octocrylene 10%

Purpose

Sunscreen

Uses

- helps prevent sunburn
- if used as directed with other sun protection measures (see Directions), decreases the risk of skin cancer and early skin aging caused by the sun

Warnings

For external use only

Do not use

- on damaged or broken skin

When using this product

- keep out of eyes. Rinse with water to remove.

Stop use and ask doctor if

- rash occurs.

Keep out of reach of children.

If product is swallowed, get medical help or contact a Poison Control Center right away.

Directions

• apply liberally 15 minutes before sun exposure
• reapply:
• after 80 minutes of swimming or sweating
• immediately after towel drying
• at least every 2 hours
• Sun Protection Measures. Spending time in the sun increases your risk of skin cancer and early skin aging. To decrease this risk, regularly use a sunscreen with a broad spectrum SPF value of 15 or higher and other sun protection measures including:
• limit time in the sun, especially from 10 a.m. - 2 p.m.
• wear long-sleeved shirts, pants, hats, and sunglasses
• children under 6 months: Ask a doctor

Other information

• protect the product in this container from excessive heat and direct sun
• may stain or damage some fabrics, materials or surfaces

Inactive ingredients

ozokerite, C12-15 alkyl benzoate, paraffin, adipic acid/diglycol crosspolymer, beeswax, octyldodecyl neopentanoate, dimethicone, neopentyl glycol diethylhexanoate, neopentyl glycol diisostearate, caprylyl glycol, tocopherol, fragrance